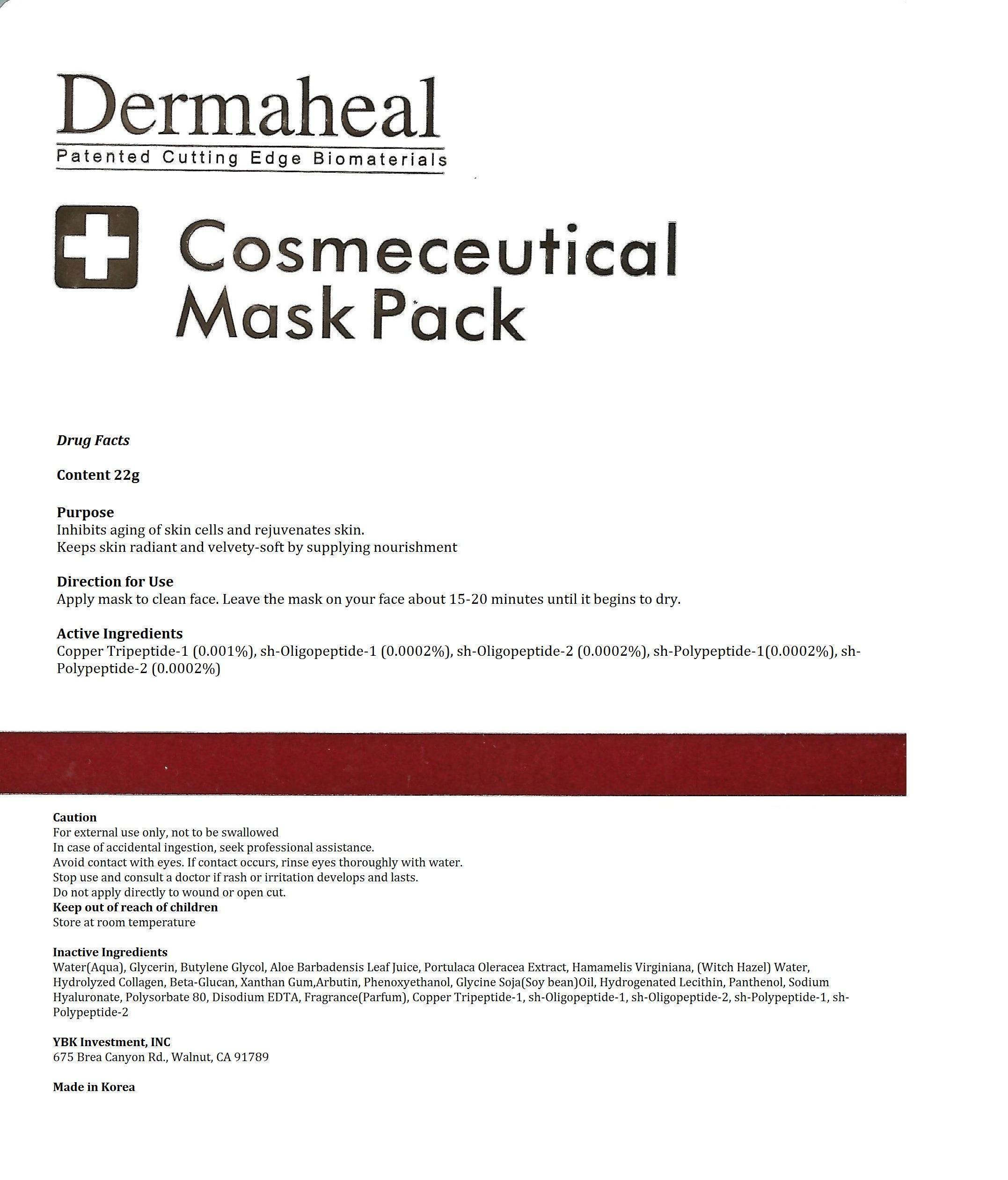 DRUG LABEL: Dermaheal Cosmeceutical Mask Pack Plus
NDC: 60709-105 | Form: PATCH
Manufacturer: YBK Investment, INC
Category: otc | Type: HUMAN OTC DRUG LABEL
Date: 20131101

ACTIVE INGREDIENTS: PREZATIDE COPPER 0.22 mg/22 g; PALMITOYL OLIGOPEPTIDE 0.044 mg/22 g; NEPIDERMIN 0.044 mg/22 g; MECASERMIN 0.044 mg/22 g; BASIC FIBROBLAST GROWTH FACTOR (HUMAN) 0.044 mg/22 g; THIOREDOXIN 0.044 mg/22 g
INACTIVE INGREDIENTS: water; GLYCERIN; ALOE VERA LEAF; PORTULACA OLERACEA LEAF; XANTHAN GUM; HAMAMELIS VIRGINIANA TOP WATER; ARBUTIN; PHENOXYETHANOL; SOYBEAN OIL; HYDROGENATED SOYBEAN LECITHIN; PANTHENOL; PEG-9 DIGLYCIDYL ETHER/SODIUM HYALURONATE CROSSPOLYMER; POLYSORBATE 80; DISODIUM EDTA-COPPER

Dermaheal Cosmeceutical Mask Pack Plus

WARNINGS

For external use only, not to be swallowed

In case of accidental ingestion, seek professional assistance.

Do not apply directly to wound or open cut.

DOSAGE AND ADMINISTRATION

one time use only, one mask pack per person

INDICATIONS AND USAGE

Apply mask to clean face. Leave the mask on your face about 15-20 minutes until it begins to dry.

Stop use and consult a doctor if rash or irritation develops and lasts.

Active Ingredients

Copper Tripeptide-1 (0.001%), sh-Oligopeptide-1 (0.0002%), sh-Oligopeptide-2 (0.0002%), sh-Polypeptide-1(0.0002%), sh-Polypeptide-2 (0.0002%)

Inactive Ingredients

Water(Aqua), Glycerin, Butylene Glycol, Aloe Barbadensis Leaf Juice, Portulaca Oleracea Extract, Hamamelis Virginiana, (Witch Hazel) Water, Hydrolyzed Collagen, Beta-Glucan, Xanthan Gum,Arbutin, Phenoxyethanol, Glycine Soja(Soy bean)Oil, Hydrogenated Lecithin, Panthenol, Sodium Hyaluronate, Polysorbate 80, Disodium EDTA, Fragrance(Parfum), Copper Tripeptide-1, sh-Oligopeptide-1, sh-Oligopeptide-2, sh-Polypeptide-1, sh-Polypeptide-2

Keep out of reach of children

Purpose

Inhibits aging of skin cells and rejuvenates skin.

Keeps skin radiant and velvety-soft by supplying nourishment